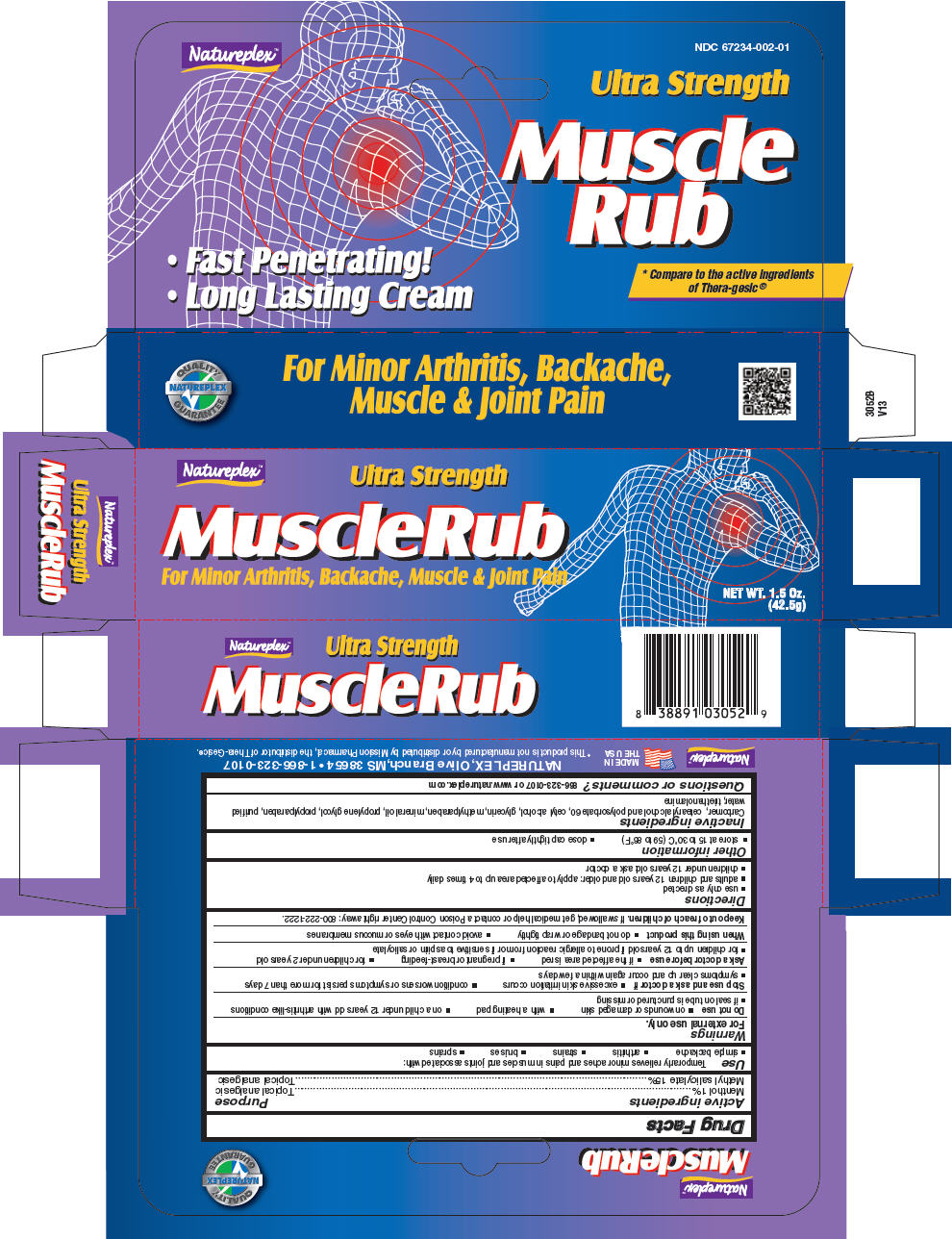 DRUG LABEL: Muscle Rub 
NDC: 67234-002 | Form: CREAM
Manufacturer: Natureplex LLC
Category: otc | Type: HUMAN OTC DRUG LABEL
Date: 20241231

ACTIVE INGREDIENTS: MENTHOL, UNSPECIFIED FORM 0.01 mg/1 g; METHYL SALICYLATE 0.15 mg/1 g
INACTIVE INGREDIENTS: CARBOMER HOMOPOLYMER TYPE C (ALLYL PENTAERYTHRITOL CROSSLINKED); CETYL ALCOHOL; CETOSTEARYL ALCOHOL; POLYSORBATE 60; GLYCERIN; METHYLPARABEN; MINERAL OIL; PROPYLENE GLYCOL; PROPYLPARABEN; TROLAMINE; WATER

Muscle Rub Ultra Strength
Topical Analgesic

Drug Facts

ACTIVE INGREDIENT

Active ingredients | Purpose
Menthol 1% | Topical analgesic
Methyl salicylate 15% | Topical analgesic

Use

Temporarily relieves minor aches and pains in muscles and joints associated with:

- simple backache
- arthritis
- strains
- bruises
- sprains

Warnings

For external use only.

Do not use

- on wounds or damaged skin
- with a heating pad
- on a child under 12 years old with arthritis-like conditions
- if seal on tube is punctured or missing

Stop use and ask a doctor if

- excessive skin irritation occurs
- condition worsens or symptoms persist for more than 7 days
- symptoms clear up and occur again within a few days

Ask a doctor before use

- if the affected area is red
- if pregnant or breast-feeding
- for children under 2 years old
- for children up to 12 years old if prone to allergic reaction from or if sensitive to aspirin or salicylate

When using this product

- do not bandage or wrap tightly
- avoid contact with eyes or mucous membranes

Keep out of reach of children. If swallowed, get medical help or contact a Poison Control Center right away: 800-222-1222.

Directions

- use only as directed
- adults and children 12 years old and older: apply to affected area up to 4 times daily
- children under 12 years old: ask a doctor

Other information

- store at 15 to 30°C (59 to 86°F)
- close cap tightly after use

Inactive ingredients

Carbomer, cetearyl alcohol and polysorbate 60, cetyl alcohol, glycerin, methylparaben, mineral oil, propylene glycol, propylparaben, purified water, triethanolamine

Questions or comments?

866-323-0107 or www.natureplex.com

PRINCIPAL DISPLAY PANEL - 42.5 g Tube Carton

Natureplex™

Ultra Strength
MuscleRub
For Minor Arthritis, Backache, Muscle & Joint Pain

NET WT. 1.5 Oz.
(42.5g)